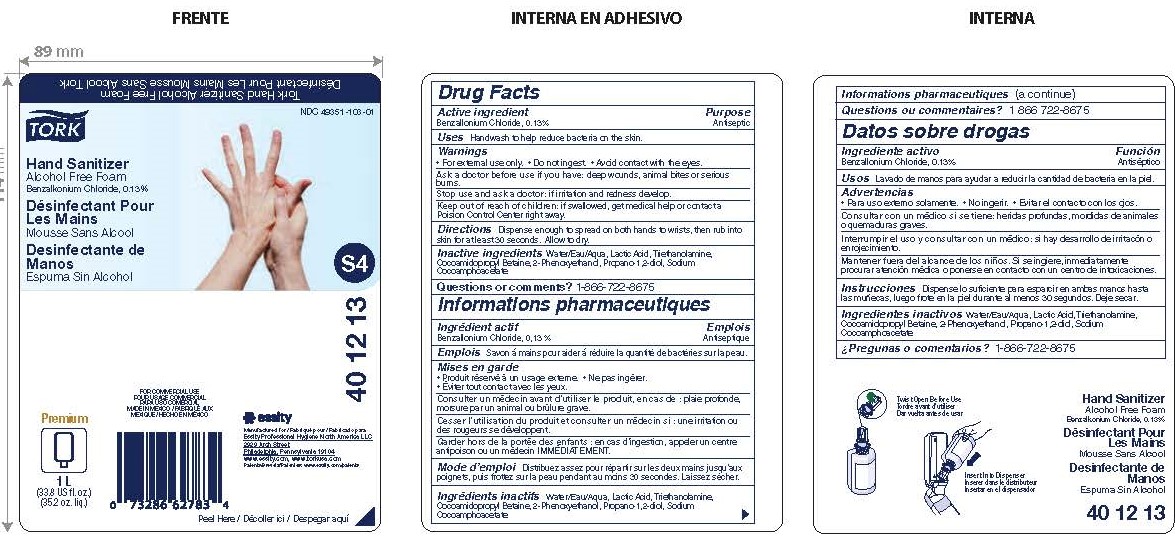 DRUG LABEL: Tork Hand Sanitizer Alcohol Free Foam
NDC: 49351-103 | Form: LIQUID
Manufacturer: Essity Professional Hygiene North America LLC
Category: otc | Type: HUMAN OTC DRUG LABEL
Date: 20240502

ACTIVE INGREDIENTS: BENZALKONIUM CHLORIDE 0.13 g/100 mL
INACTIVE INGREDIENTS: WATER; LACTIC ACID; TROLAMINE; COCAMIDOPROPYL BETAINE; PHENOXYETHANOL; PROPYLENE GLYCOL; SODIUM COCOAMPHOACETATE

49351-103

Drug Facts

Active ingredient

Benzalkonium chloride, 0.13%

Purpose

Antiseptic

Uses

Handwash to help reduce bacteria on the skin.

Warnings

- For external use only
- Do not ingest
- Avoid contact with the eyes

Ask a doctor before use if you have:

Deep wounds, animal bites or serious burns

Stop use and ask a doctor:

If irritation and redness develop.

Keep out of reach of children:

If swallowed, get medical help or contact a Poison Control Center right away

Directions

Dispense enough to spread on both hands to wrists, then rub into the skin for at least 30 seconds. Allow to dry.

Inactive ingredients

Water/Eau/Aqua, Lactic acid, Triethanolamine, Cocoamidopropyl betaine, 2-Phenoxyethanol, Propano-1,2-diol, Sodium cocoamphoacetate.

Questions or Comments?

1-866-722-8675

PACKAGE LABEL

TORK®

Hand Sanitizer

Alcohol Free Foam

Benzalkonium Chloride, 0.13%

NDC 49351-103-01

Manufactured for Essity Professional Hygiene North America, LLC

2929 Arch Street

Philadelphia, PA 19104

www essity.com, www.torkusa.com

For Commercial use

Made in Mexico

Premium

1 L

(33.8 US fl. oz.)

(35.2 oz. liq.)